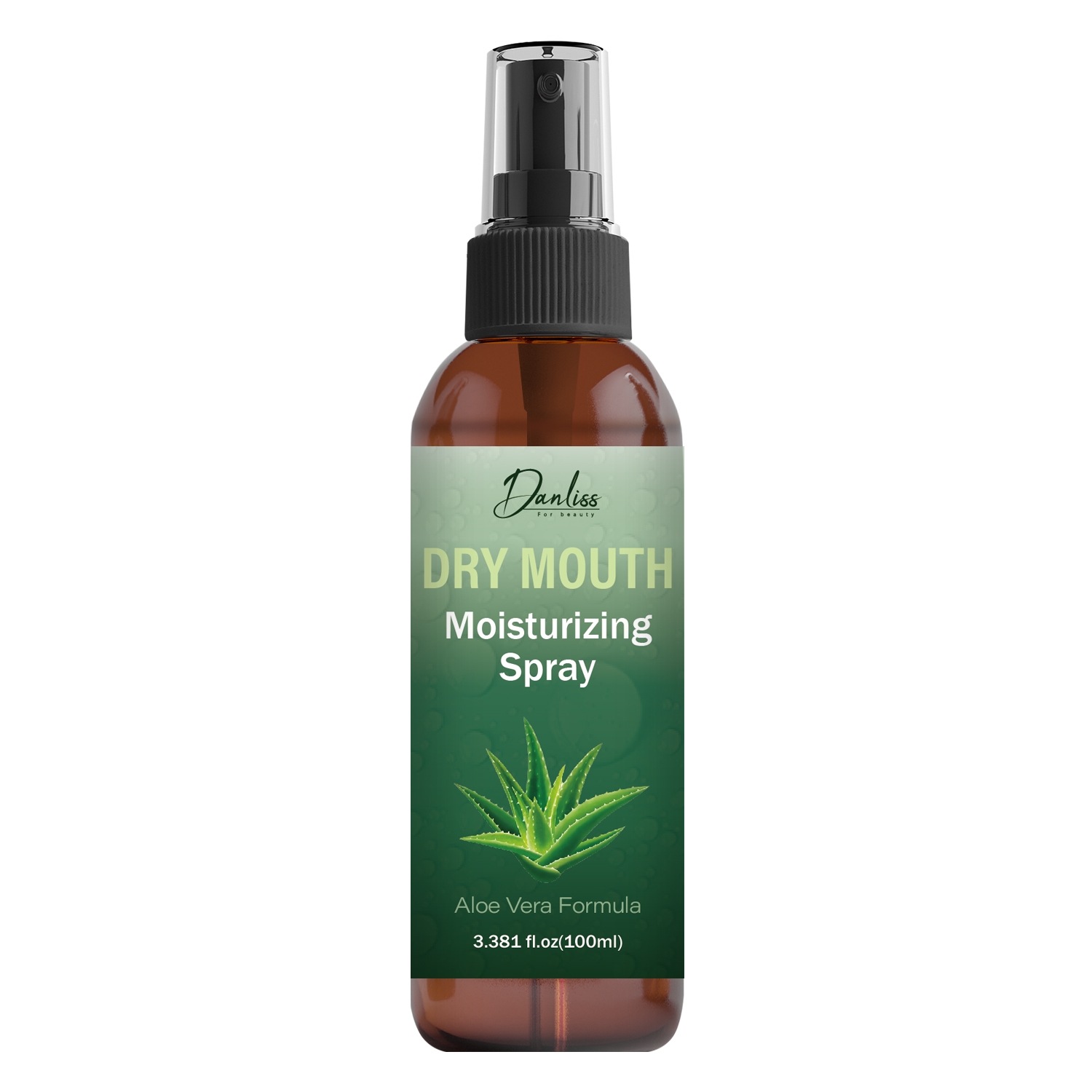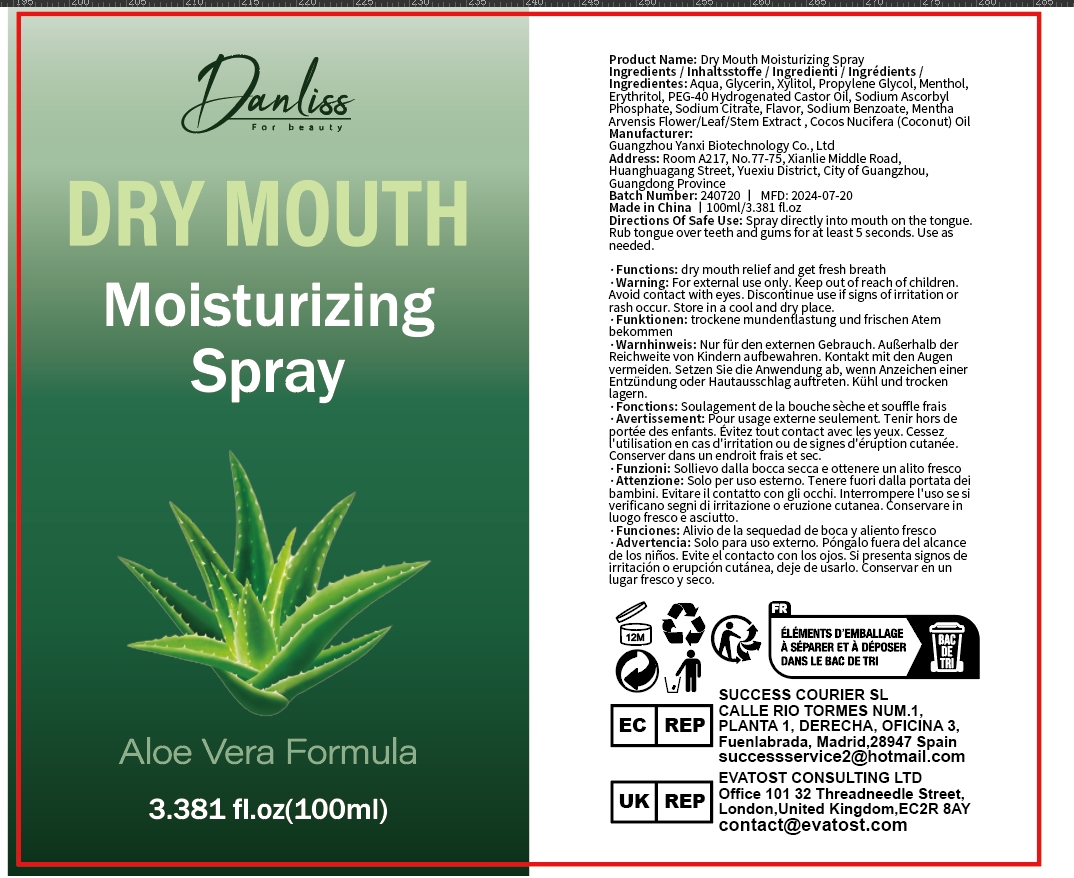 DRUG LABEL: Dry Month MoisturizingSpray
NDC: 84025-160 | Form: SPRAY
Manufacturer: Guangzhou Yanxi Biotechnology Co.. Ltd
Category: otc | Type: HUMAN OTC DRUG LABEL
Date: 20240818

ACTIVE INGREDIENTS: XYLITOL 3 mg/100 mL; GLYCERIN 5 mg/100 mL
INACTIVE INGREDIENTS: WATER

DOSAGE AND ADMINISTRATION

Spray for moisturizing and caring for the mouth

WARNINGS

Keep out of children

INACTIVE INGREDIENT

AQUA

INDICATIONS AND USAGE

For daily oral care

Keep out of children

PURPOSE

Effectively moisturizes the mouth and removes bad breath